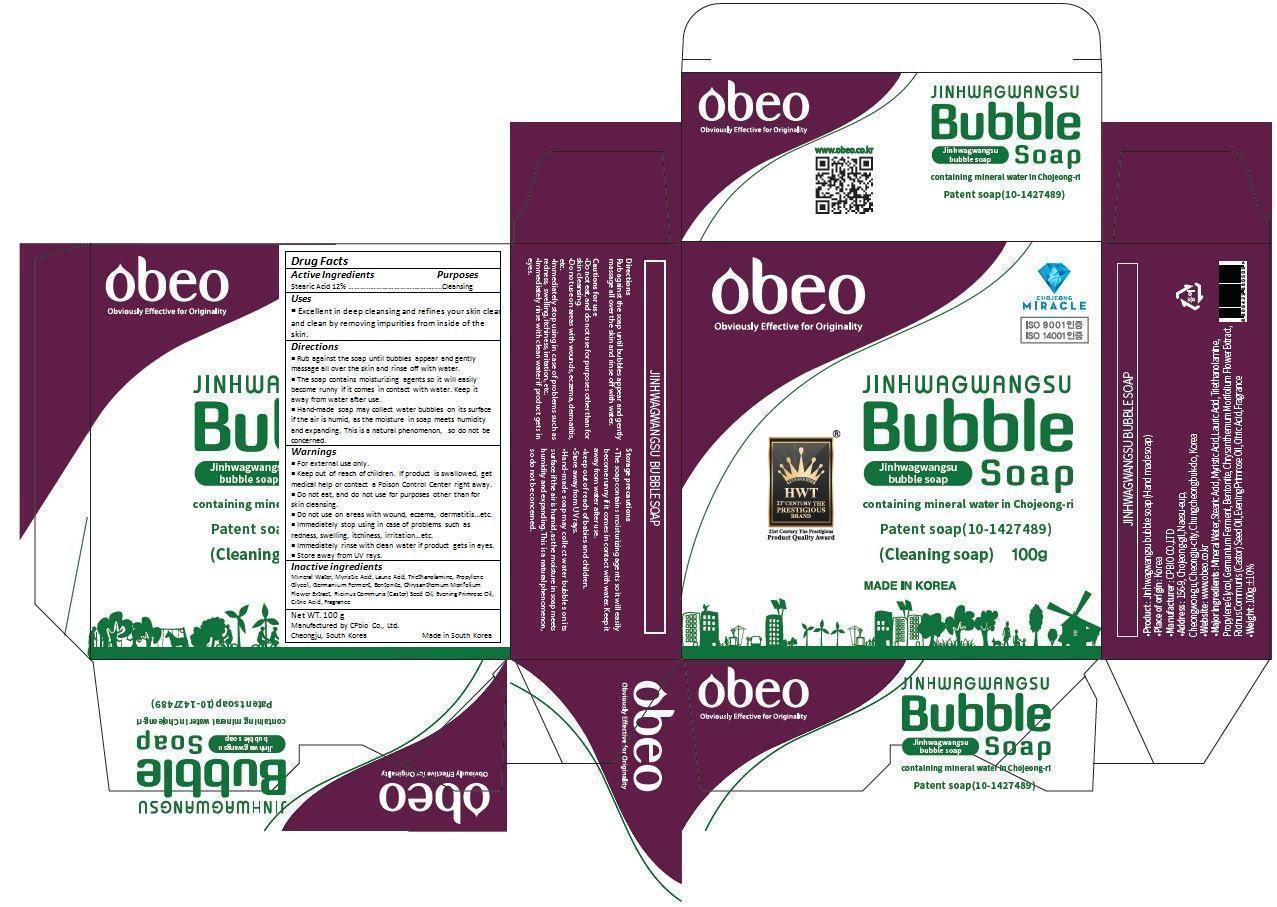 DRUG LABEL: Jinhwagwangsu Bubble
NDC: 69871-001 | Form: SOAP
Manufacturer: CPbio Co., Ltd
Category: otc | Type: HUMAN OTC DRUG LABEL
Date: 20150601

ACTIVE INGREDIENTS: STEARIC ACID 120 mg/1 g
INACTIVE INGREDIENTS: WATER; MYRISTIC ACID; LAURIC ACID; TROLAMINE; PROPYLENE GLYCOL; BENTONITE; CHRYSANTHEMUM X MORIFOLIUM FLOWER; CASTOR OIL; EVENING PRIMROSE OIL; CITRIC ACID MONOHYDRATE

Drug Facts

ACTIVE INGREDIENT

STEARIC ACID 12.00%

PURPOSE

Cleansing

INDICATIONS AND USAGE

Excellent in deep cleansing and refines your skin clear
and clean by removing impurities from inside of the
skin.

DOSAGE AND ADMINISTRATION

Rub against the soap until bubbles appear and gently massage all over the skin and rinse off with water.

The soap contains moisturizing agents so it will easily become runny if it comes in contact with water. Keep it
away from water after use.

Hand-made soap may collect water bubbles on its surface if the air is humid, as the moisture in soap meets humidity and expanding. This is a natural phenomenon, so do not be concerned.

WARNINGS

For external use only.

Do not eat, and do not use for purposes other than for skin cleansing.

Do not use on areas with wound, eczema, dermatitis...etc.

Immediately stop using in case of problems such as redness, swelling, itchiness, irritation…etc.

Immediately rinse with clean water if product gets in eyes.

Store away from UV rays.

Keep out of reach of children. If product is swallowed, get medical help or contact a Poison Control Center right away.

INACTIVE INGREDIENT

Mineral Water, Myristic Acid, Lauric Acid, Triethanolamine, Propylene Glycol, Germanium Ferment, Bentonite, Chrysanthemum Morifolium Flower Extract, Ricinus Communis (Castor) Seed Oil, Evening Primrose Oil, Citric Acid, Fragrance